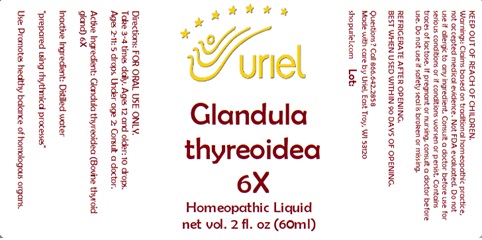 DRUG LABEL: Glandula thyreoidea 6X
NDC: 48951-5137 | Form: LIQUID
Manufacturer: Uriel Pharmacy Inc.
Category: homeopathic | Type: HUMAN OTC DRUG LABEL
Date: 20240417

ACTIVE INGREDIENTS: THYROID, UNSPECIFIED 6 [hp_X]/1 mL
INACTIVE INGREDIENTS: WATER

Glandula thyreoidea 6X

INDICATIONS AND USAGE

Directions: FOR ORAL USE ONLY.

DOSAGE AND ADMINISTRATION

Take 3-4 times daily. Ages 12 and older: 10 drops. Ages 2-11: 5 drops. Under age 2: Consult a doctor.

Active Ingredient: Glandula thyreoidea (Bovine thyroid gland) 6X

Inactive Ingredient: Distilled water

"prepared using rhythmical processes"

PURPOSE

Use: Promotes healthy balance of homologous organs.

KEEP OUT OF REACH OF CHILDREN.

WARNINGS

Warnings: Claims based on traditional homeopathic practice, not accepted medical evidence. Not FDA evaluated. Do not use if allergic to any ingredient. Consult a doctor before use for serious conditions or if conditions worsen or persist. If pregnant or nursing, consult a doctor before use. Do not use if safety seal is broken or missing.

REFRIGERATE AFTER OPENING.
BEST WHEN USED WITHIN 90 DAYS OF OPENING.

QUESTIONS

Questions? Call 866.642.2858 Made with care by Uriel, East Troy, WI 53120 shopuriel.com Lot: